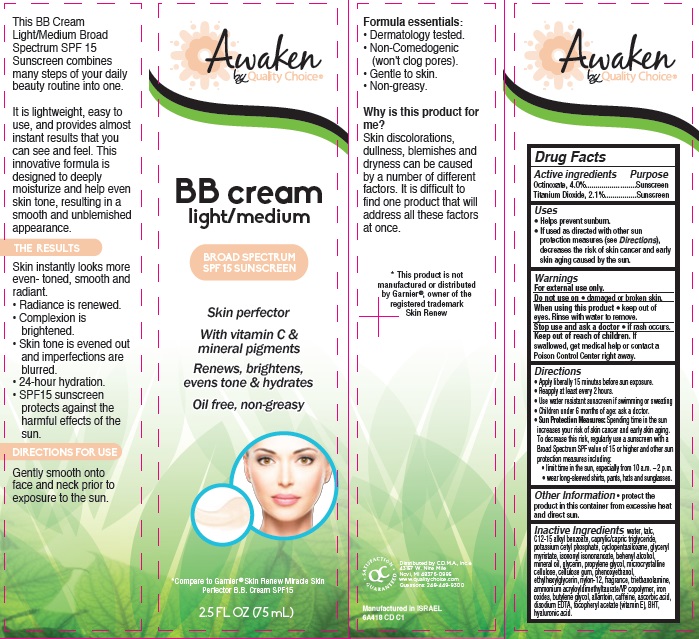 DRUG LABEL: Awaken Skin Perfector BB Broad Spectrum SPF 15 Sunscreen Light Medium
NDC: 63868-252 | Form: CREAM
Manufacturer: Chain Drug Marketing Association
Category: otc | Type: HUMAN OTC DRUG LABEL
Date: 20140918

ACTIVE INGREDIENTS: OCTINOXATE 4 g/100 mL; TITANIUM DIOXIDE 2.1 g/100 mL
INACTIVE INGREDIENTS: WATER; TALC; ALKYL (C12-15) BENZOATE; MEDIUM-CHAIN TRIGLYCERIDES; POTASSIUM CETYL PHOSPHATE; CYCLOMETHICONE 5; GLYCERYL MYRISTATE; ISONONYL ISONONANOATE; DOCOSANOL; MINERAL OIL; GLYCERIN; PROPYLENE GLYCOL; CELLULOSE, MICROCRYSTALLINE; CARBOXYMETHYLCELLULOSE SODIUM; PHENOXYETHANOL; ETHYLHEXYLGLYCERIN; NYLON-12; TROLAMINE; AMMONIUM ACRYLOYLDIMETHYLTAURATE/VP COPOLYMER; FERROUS OXIDE; BUTYLENE GLYCOL; ALLANTOIN; CAFFEINE; ASCORBIC ACID; EDETATE DISODIUM; .ALPHA.-TOCOPHEROL ACETATE; BUTYLATED HYDROXYTOLUENE; HYALURONIC ACID

Awaken by Quality Choice® BB Cream Light/Medium Broad Spectrum SPF 15 Sunscreen

Active ingredients

Octinoxate, 4.0%
Titanium Dioxide, 2.1%

Purpose

Sunscreen

Uses

- Helps prevent sunburn.
- If used as directed with other sun protection measures (see Directions), decreases the risk of skin cancer and early skin aging caused by the sun.

Warnings

For external use only.

Do not use on

- damaged or broken skin.

When using this product

- keep out of eyes. Rinse with water to remove.

Stop use and ask a doctor

- if rash occurs.

Keep Out of Reach of Children

If swallowed, get medical help or contact a Poison Control Center right away.

Directions

- Apply liberally 15 minutes before sun exposure.
- Reapply at least every 2 hours.
- Use water resistant sunscreen if swimming or sweating.
- Children under 6 months of age: ask a doctor.
- Sun Protection Measures: Spending time in the sun increases your risk of skin cancer and early skin aging. To decrease this risk, regularly use a sunscreen with a Broad Spectrum SPF value of 15 or higher and other sun protection measures including:
  - limit time in the sun, especially from 10 a.m. – 2 p.m.
  - wear long-sleeved shirts, pants, hats and sunglasses.

Other Information

- protect the product in this container from excessive heat and direct sun

Inactive Ingredients

water, talc, C12-15 alkyl benzoate, caprylic/capric triglyceride, potassium cetyl phosphate, cyclopentasiloxane, glyceryl miristate, isononyl isononanoate, behenyl alcohol, mineral oil, glycerin, propylene glycol, microcrystalline cellulose, cellulose gum, phenoxyethanol, ethylhexylglycerin, nylon-12, fragrance, triethanolamine, ammonium acryloyldimethyltaurate/VP copolymer, iron oxides, butylene glycol, allantoin, caffeine, ascorbic acid, disodium EDTA, tocopheryl acetate (vitamin E), BHT, hyaluronic acid.

Package/Label Principal Display Panel

Awaken by Quality Choice®
BB cream
light/medium

Broad Spectrum
SPF 15 Sunscreen

Skin perfector

With vitamin C & mineral pigments

Renews, brightens, evens tone & hydrates

Oil free, non-greasy

*Compare to Garnier® Skin Renew Miracle Skin Perfector B.B. Cream SPF15

2.5 FL OZ (75 mL)

This BB Cream Light/Medium Broad Spectrum SPF 15 Sunscreen combines many steps of your daily beauty routine into one.

It is lightweight, easy to use, and provides almost instant results that you can see and feel. This innovative formula is designed to deeply moisturize and help even skin tone, resulting in a smooth and unblemished appearance.

The Results
Skin instantly looks more even-toned, smooth and radiant.

- Radiance is renewed.
- Complexion is brightened.
- Skin tone is evened out and imperfections are blurred.
- 24-hour hydration.
- SPF15 sunscreen protects against the harmful effects of the sun.

Directions For Use
Gently smooth onto face and neck prior to exposure to the sun.

Formula Essentials:

- Dermatology tested.
- Non-Comedogenic (won’t clog pores).
- Gentle to skin.
- Non-greasy.

Why is this product for me?
Skin discolorations, dullness, blemishes and dryness can be caused by a number of different factors. It is difficult to find one product that will address all these factors at once.

This product is not manufactured or distributed by Garnier®, owner of the registered trademark Skin Renew

Satisfaction Guaranteed

Distributed by C.D.M.A., Inc.©
43157 W. Nine Mile
Novi, MI 48376-0995
www.qualitychoice.com
Questions: 248-449-9300

Manufactured in ISRAEL
6A418 CD C1

Carton Label